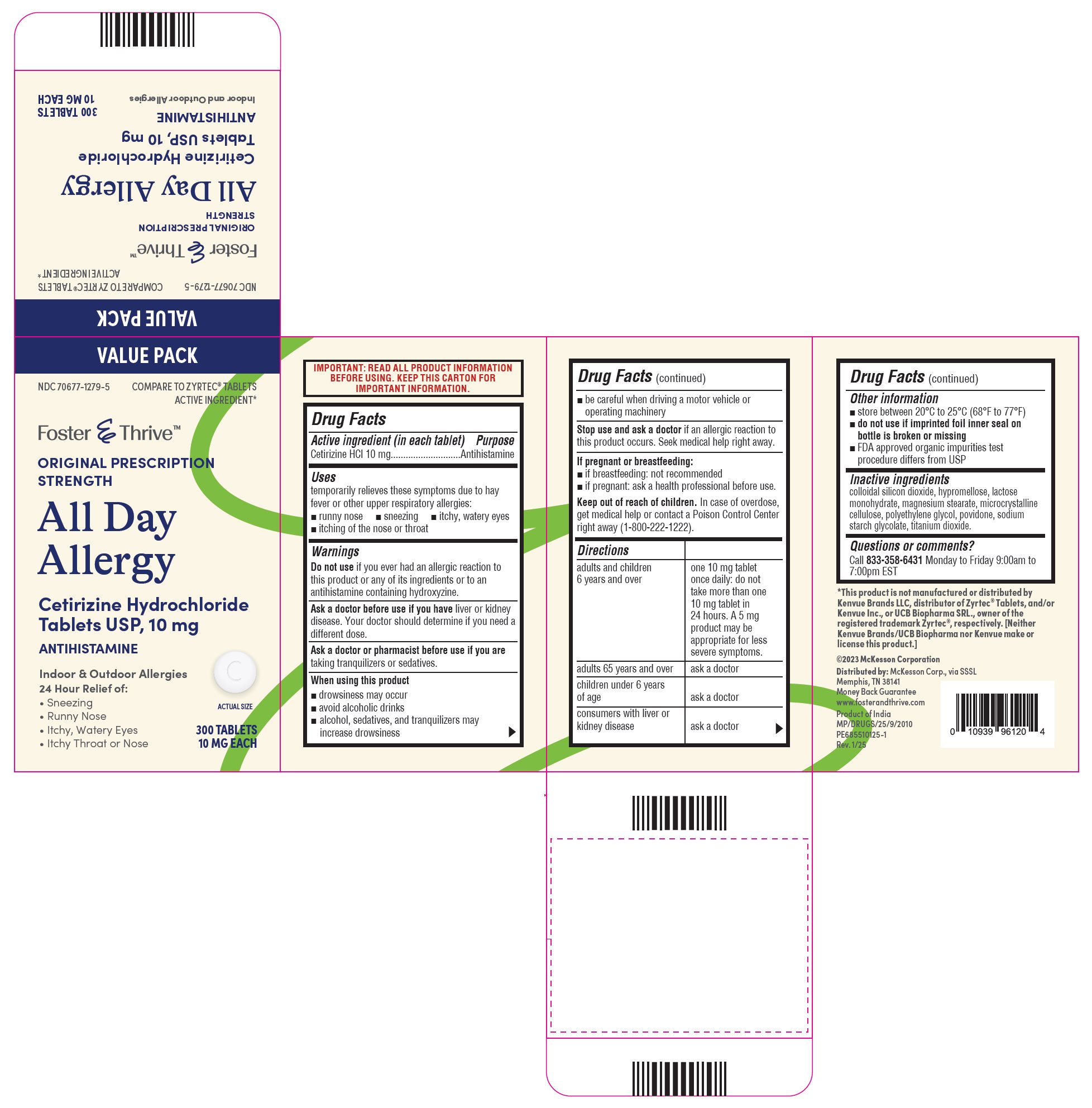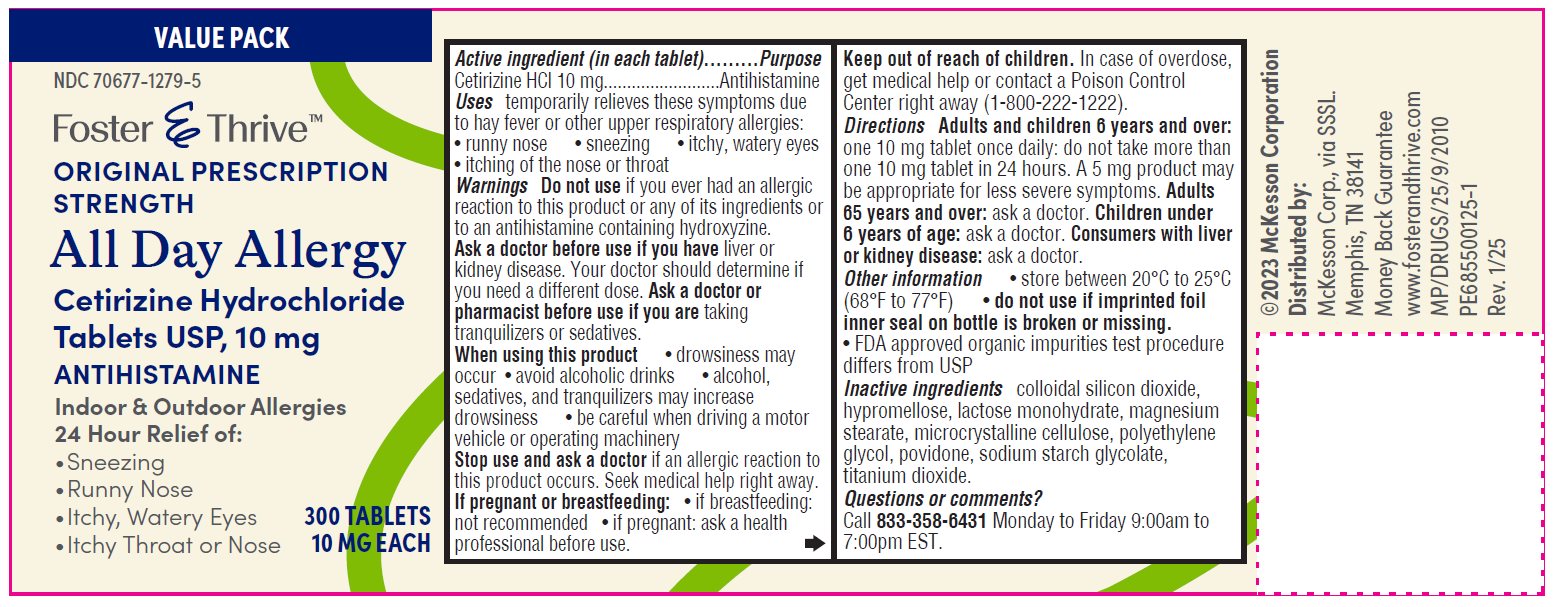 DRUG LABEL: Cetirizine HCl
NDC: 70677-1279 | Form: TABLET
Manufacturer: Strategic Sourcing Services LLC
Category: otc | Type: HUMAN OTC DRUG LABEL
Date: 20250404

ACTIVE INGREDIENTS: CETIRIZINE HYDROCHLORIDE 10 mg/1 1
INACTIVE INGREDIENTS: SILICON DIOXIDE; HYPROMELLOSE, UNSPECIFIED; LACTOSE MONOHYDRATE; MAGNESIUM STEARATE; MICROCRYSTALLINE CELLULOSE; POLYETHYLENE GLYCOL, UNSPECIFIED; POVIDONE K30; SODIUM STARCH GLYCOLATE TYPE A; TITANIUM DIOXIDE

Drug Facts

ACTIVE INGREDIENT

Cetirizine HCl 10 mg

PURPOSE

Antihistamine

INDICATIONS AND USAGE

Temporarily relieves these symptoms due to hay fever or other upper respiratory allergies:

- runny nose,
- sneezing,
- itchy, watery eyes,
- itching of the nose or throat

Do not use if you have ever had an allergic reaction to this product or any of its ingredients or an antihistamine containing hydroxyzine.

Ask a doctor before use if you have liver or kidney disease.

Your doctor should determine if you need a different dose.

Ask a doctor or pharmacist before use if you are taking tranquilizers or sedatives

When using this product

- drowsiness may occur
- avoid alcoholic drinks
- alcohol, sedatives, and tranquilizers may increase drowsiness
- be careful when driving a motor vehicle or operating machinery

Stop use and ask a doctor if an allergic reaction to this product occurs. Seek medical help right away.

If pregnant or breastfeeding:

- If breastfeeding: not recommended
- if pregnant: ask a health professional before use.

Keep out of reach of children.

In case of overdose, get medical help or contact a Poison Control Center right away (1-800-222-1222).

DOSAGE AND ADMINISTRATION

Cetirizine Hydrochloride Tablets, USP 10 mg

adults and children 6 years and over | one 10 mg tablet once daily; do not take more than one 10 mg tablet in 24 hours.; A 5 mg product may be appropriate for less severe symptoms.
adults 65 years and over | ask a doctor
children under 6 years of age | ask a doctor
consumers with liver or kidney disease | ask a doctor

Other information

- store between 20°C to 25°C (68°F to 77°F)
- do not use if imprinted foil inner seal on bottle is broken or missing.
- FDA approved organic impurities test procedure differs from USP

INACTIVE INGREDIENT

colloidal silicon dioxide, hypromellose, lactose monohydrate, magnesium stearate, microcrystalline cellulose, polyethylene glycol, povidone, sodium starch glycolate, titanium dioxide.

Questions or comments?

Call 833-358-6431 Monday to Friday 9:00am to 7:00pm EST

Manufactured by:

Glenmark Pharmaceuticals Limited

Pithampur, Madhya Pradesh 454775, India

Distributed by:

McKesson Corp. via SSSL

Memphis, TN 38141

www.fosterandthrive.com

Product of India

April 2025

Package/Label Principal Display Panel

Container label

NDC 70677-1279-5

10 mg - 300 Tablets

Package/Label Principal Display Panel

Carton label

NDC 70677-1279-5

10 mg- 300 Tablets